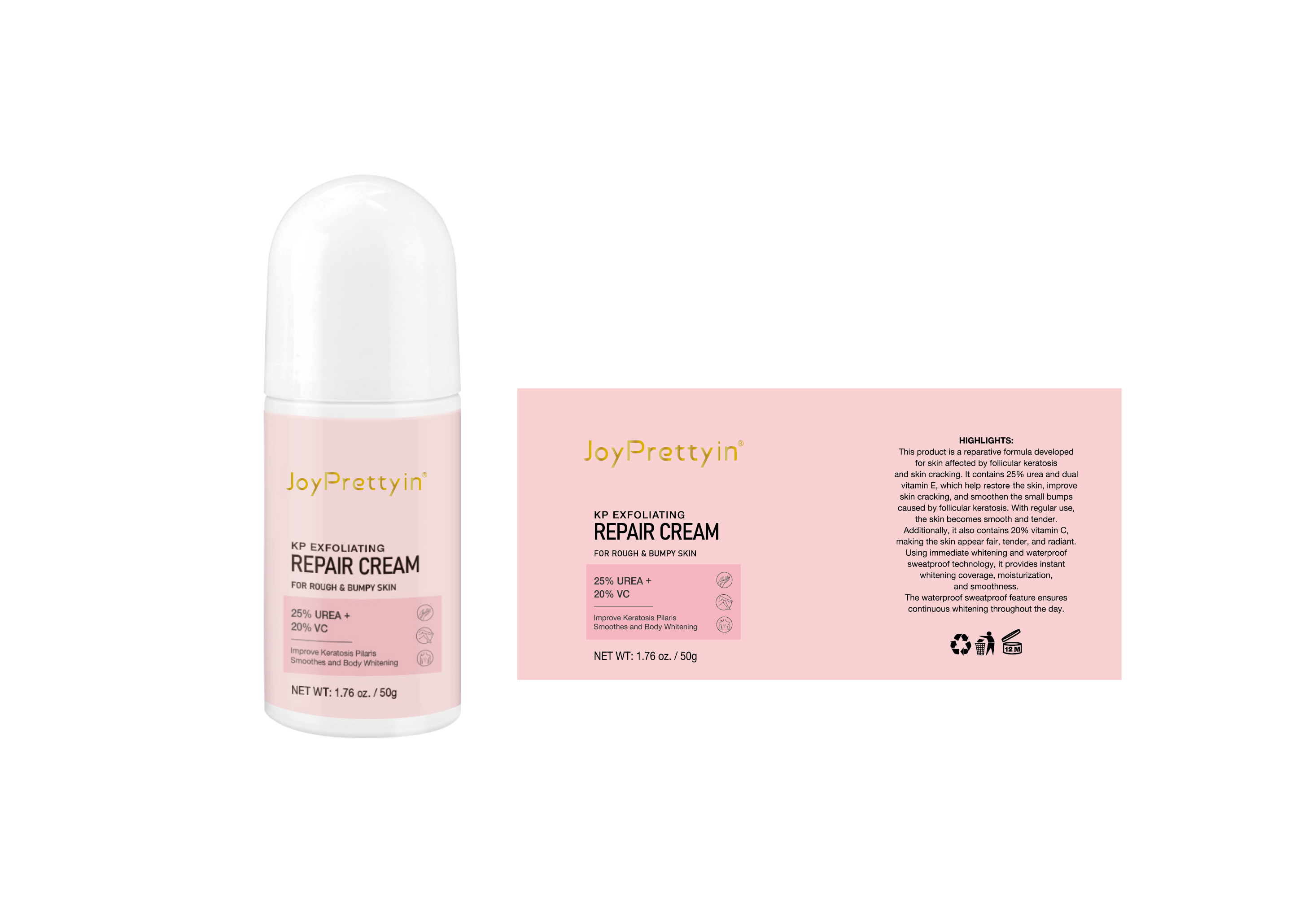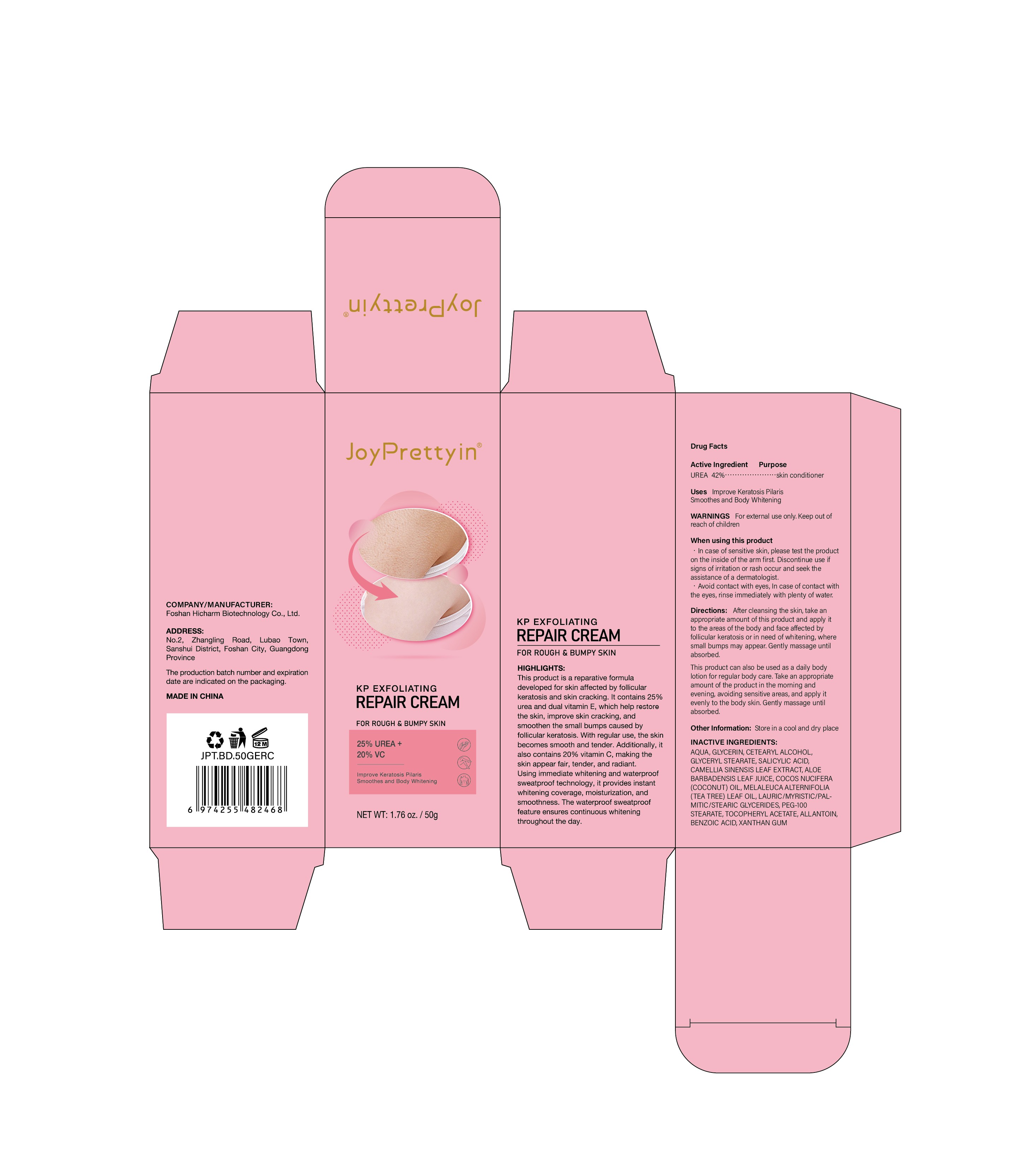 DRUG LABEL: Joypretty Kp Exfoliating Repair Cream
NDC: 84186-009 | Form: CREAM
Manufacturer: Guangzhou Bonnieco Cosmetics Co., Ltd
Category: otc | Type: HUMAN OTC DRUG LABEL
Date: 20240401

ACTIVE INGREDIENTS: UREA 25 g/100 g
INACTIVE INGREDIENTS: WATER; ETHYLHEXYL PALMITATE; PHENOXYETHANOL; GLYCERETH-26; ETHYLHEXYLGLYCERIN; TOCOPHEROL; ALKYL (C12-15) BENZOATE; CARBOMER HOMOPOLYMER, UNSPECIFIED TYPE; ASCORBIC ACID; GLYCERIN

84186-009

Active Ingredient

UREA 25%

Purpose

Chicken Skin Repair

Use

Uses lmprove Keratosis PilarisSmoothes and Body Whitening

Warnings

For external use only. Keep out ofreach of children

Do not use

ln case of sensitive skin, please test the producton the inside of the arm first. Discontinue use ifsigns of irritation or rash occur and seek theassistance of a dermatologist.- Avoid contact with eyes, In case of contact withthe eyes, rinse immediately with plenty of water.

When Using

In case of contact with the eyes, rinse immediately with plenty of water.

Stop Use

If discomfort arises, please immediately stop using the product and seek the assistance of a dermatologist.

Ask Doctor

If discomfort arises, please immediately stop using the product and seek the assistance of a dermatologist.

Keep Oot Of Reach Of Children

Keep out of reach of children. If swallowed call emergency services.

Directions

After cleansing the skin, take an appropriate amount of this product and apply it to the areas of the body and face affected by follicular keratosis or in need of whitening, where small bumps may appear. Gently massage until absorbed.

This product can also be used as a daily body lotion for regular body care. Take an appropriate amount of the product in the morning and evening, avoiding sensitive areas, and apply it evenly to the body skin. Gently massage until absorbed.

Other information

Store in a cool and dry place

Inactive ingredients

AQUA, UREA, ASCORBIC ACID, GLYCERIN, TOCOPHEROL, ETHYLHEXYL PALMITATE, GLYCERETH-26, C12-15 ALKYL BENZOATE, PHENOXYETHANOL, CARBOMER, ETHYLHEXYLGLYCERIN